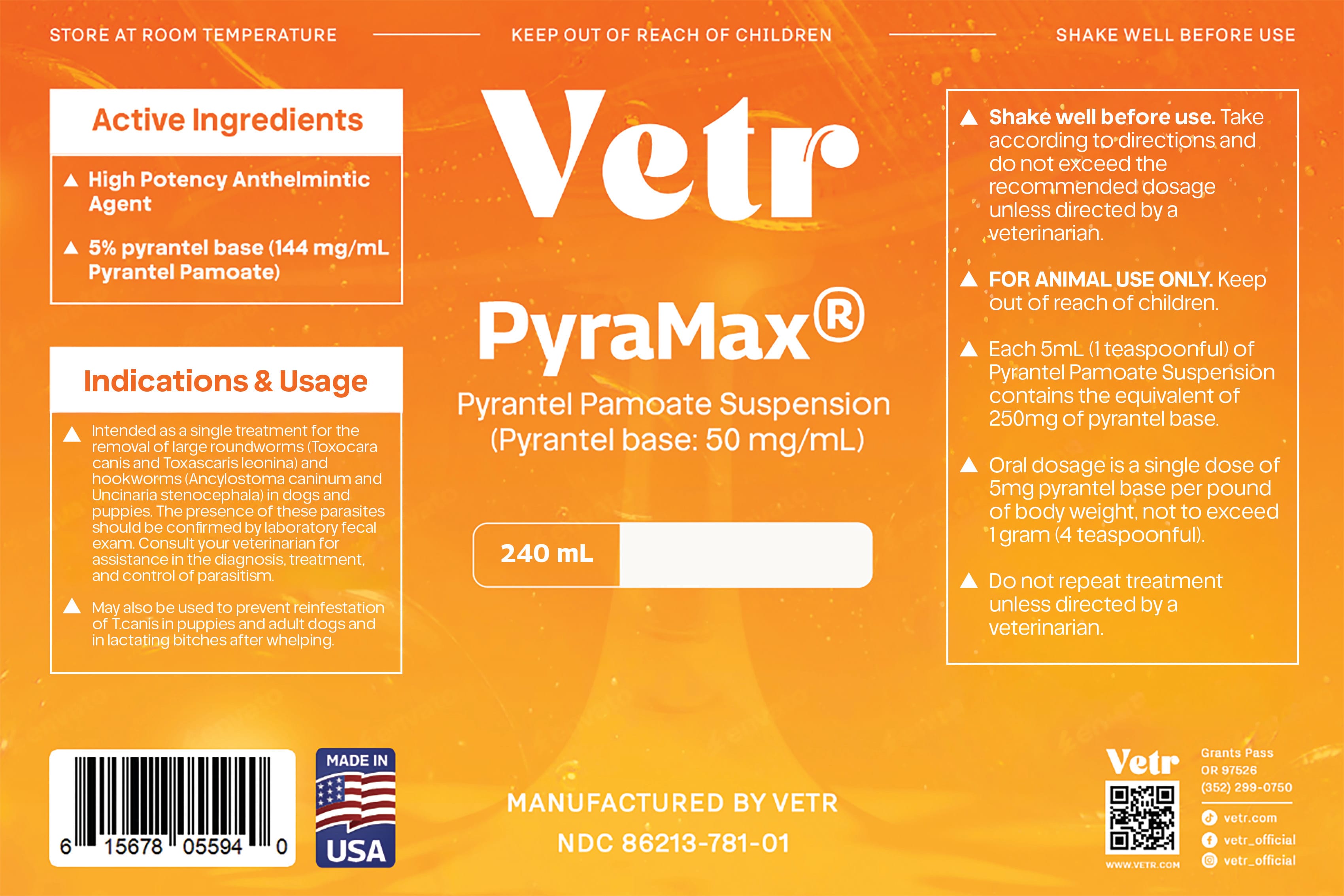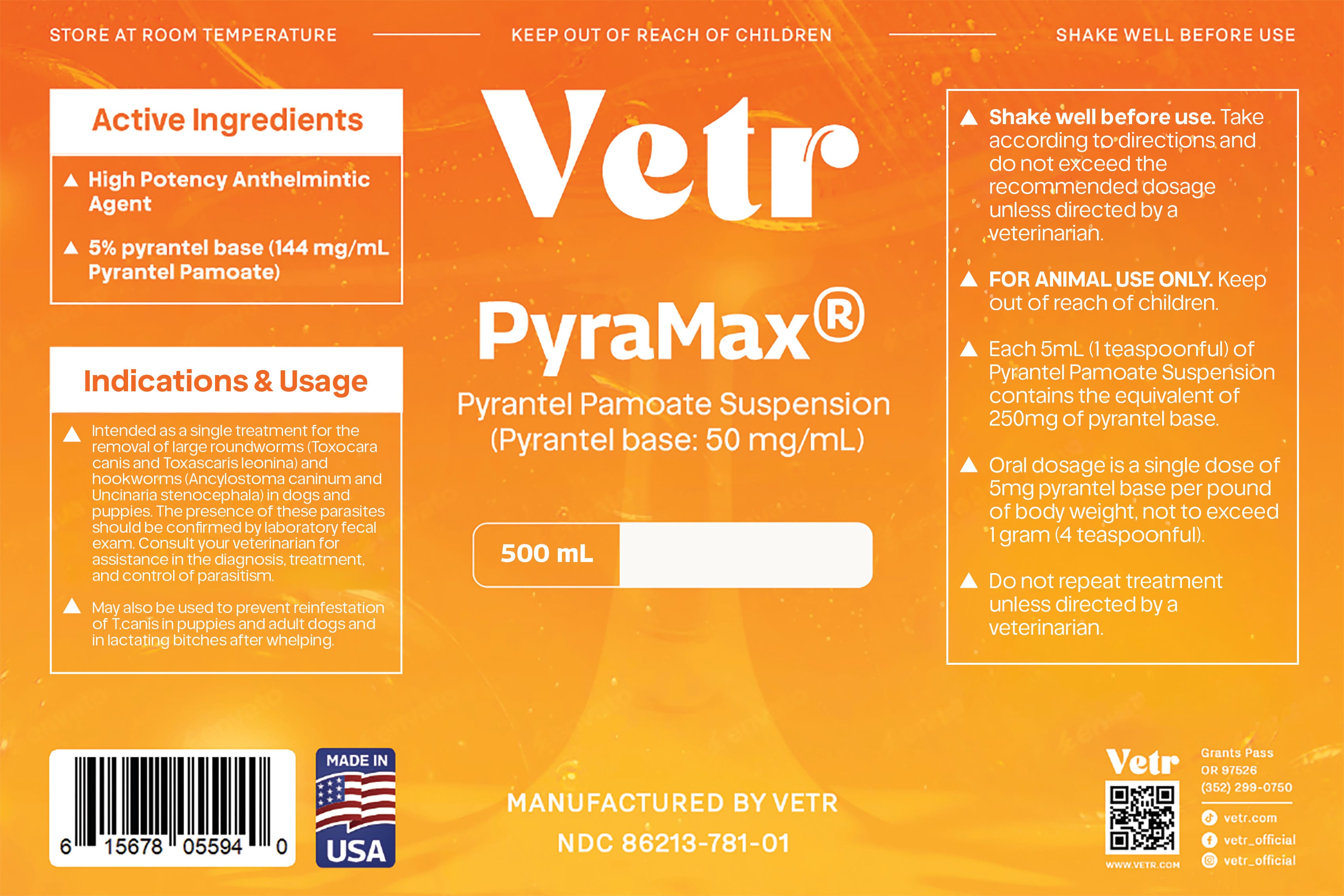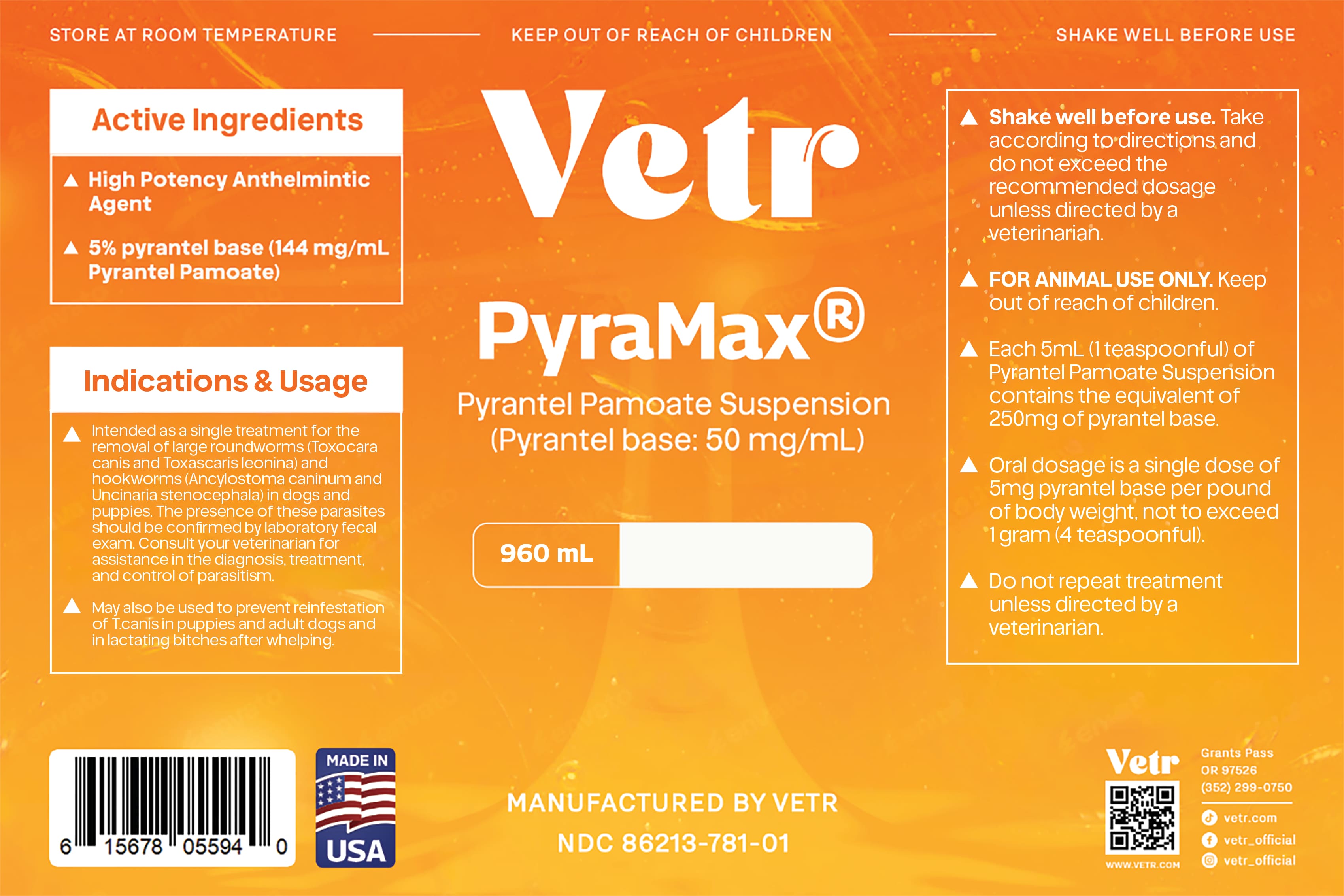 DRUG LABEL: PyraMax
NDC: 86213-781 | Form: SUSPENSION
Manufacturer: Vetr, LLC
Category: animal | Type: OTC ANIMAL DRUG LABEL
Date: 20260226

ACTIVE INGREDIENTS: PYRANTEL PAMOATE 50 mg/1 mL
INACTIVE INGREDIENTS: CITRIC ACID; POTASSIUM SORBATE; WATER

PyraMax Pyrantel Pamoate Suspension (50 mg/mL pyrantel base)

WARNINGS AND PRECAUTIONS

- Keep this medication in a secure location out of reach of dogs, cats, and other animals to prevent accidental ingestion or overdose
- Keep this and all medications out of reach of children.
- In case of accidental overdose, seek professional assistance or contact a Poison Control Center immediately.
- If your pet is pregnant or has liver disease, do not take this product unless directed by a veterinarian.

- Shake well before use.
- For the removal of large roundworms (Toxocara canis and Toxascaris leonina) and hookworms (Ancylostoma caninum and Uncinaria stenocephala) in dogs and puppies. The presence of these parasites should be confirmed by laboratory fecal exam. Consult your veterinarian for assistance in the diagnosis, treatment, and control of parasitism. Oral dosage is a single dose of 5 milligrams of pyrantel base per pound, or 11 milligrams per kilogram, of body weight not to exceed 1 gram.
- Take only according to directions and do not exceed the recommended dosage unless directed by a veterinarian. Medication should only be taken one time as a single dose, do not repeat treatment unless directed by a veterinarian. When one pet in a household has worms, the entire household should be treated unless otherwise advised. See WARNINGS. If any worms other than roundworms or hookworms are present before or after treatment, consult a veterinarian. If any symptoms or worms are still present after treatment, consult a veterinarian.
- Pyramax suspension may also be used to prevent reinfestation of T. canis in puppies and adult dogs and in lactating bitches after whelping.

DOSAGE AND ADMINISTRATION

Each mL of Pyrantel Pamoate Oral Suspension contains the equivalent of 50 mg of Pyrantel Base (as Pyrantel Pamoate).

ACTIVE INGREDIENT

Each mL of Pyrantel Pamoate Oral Suspension contains the equivalent of 50 mg of Pyrantel Base (as Pyrantel Pamoate).

INACTIVE INGREDIENT

Citric acid, potassium sorbate, purified water, glycerin, sodium benzoate, sucralose, natural flavor

INDICATIONS AND USAGE

For the treatment of pinworms